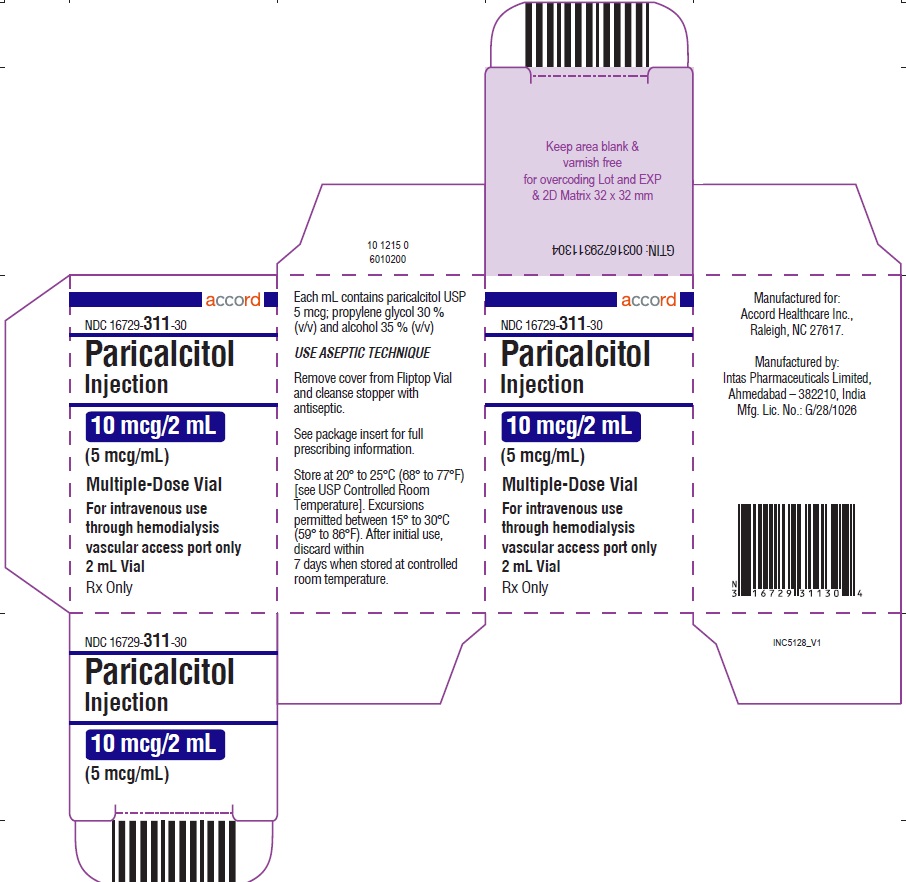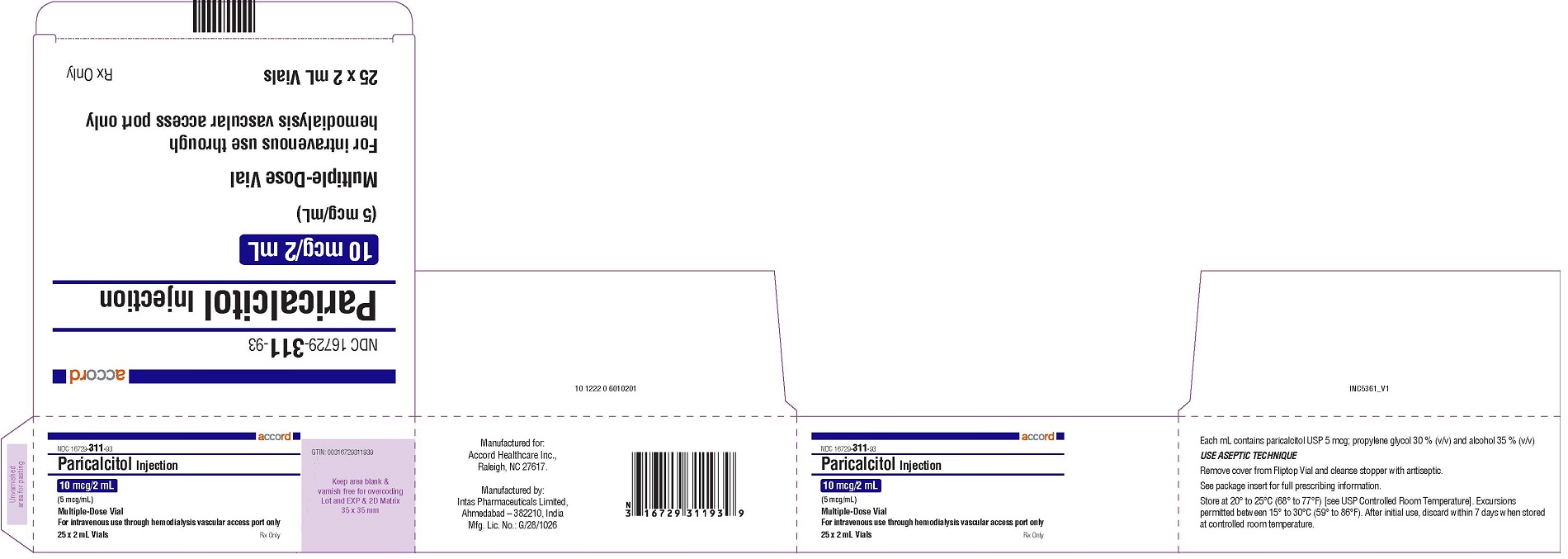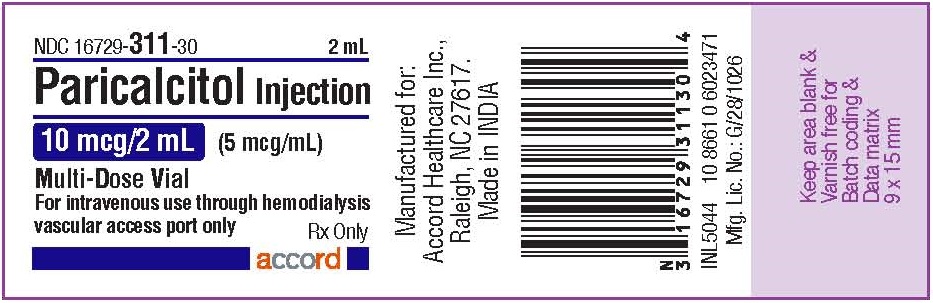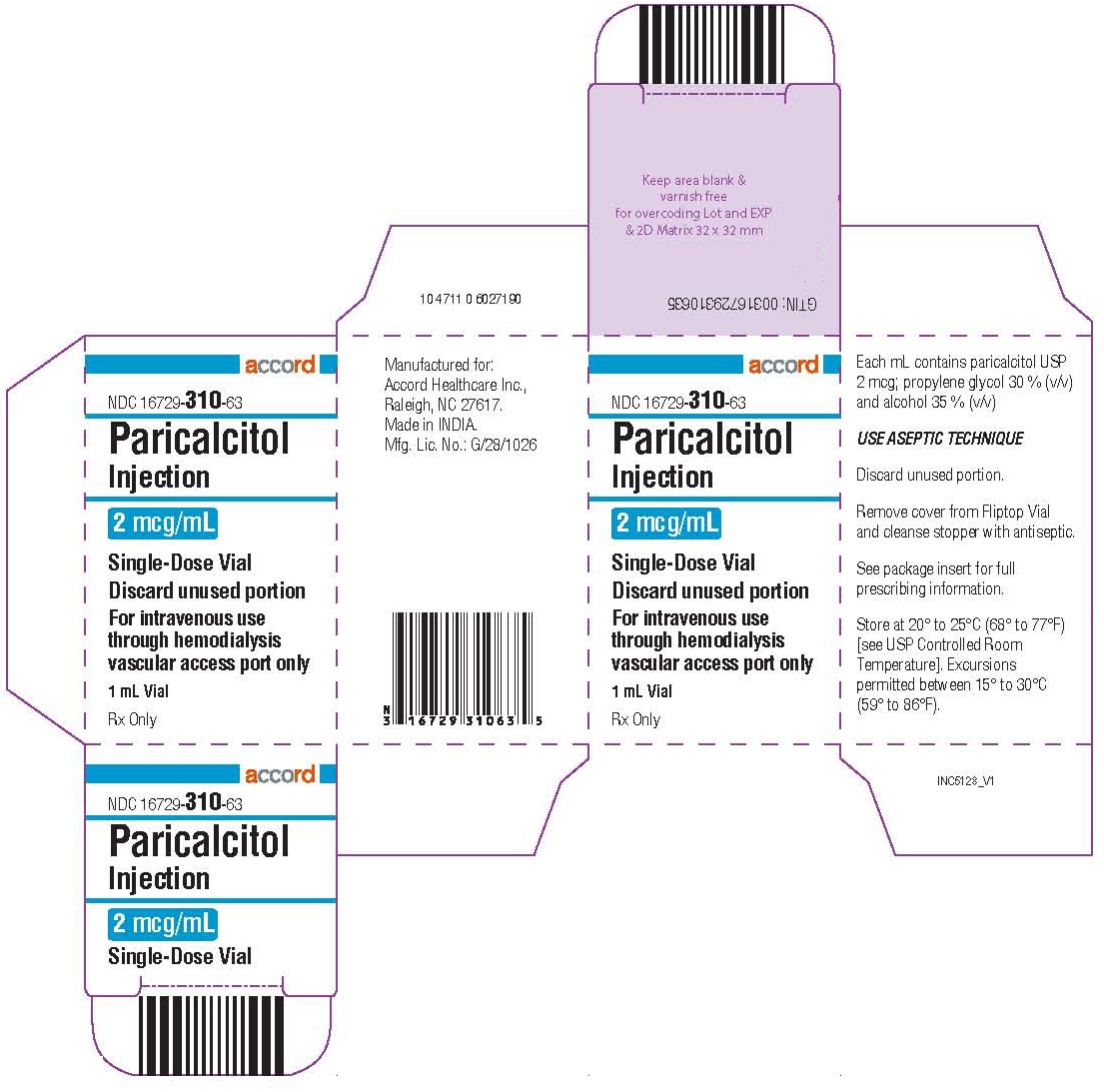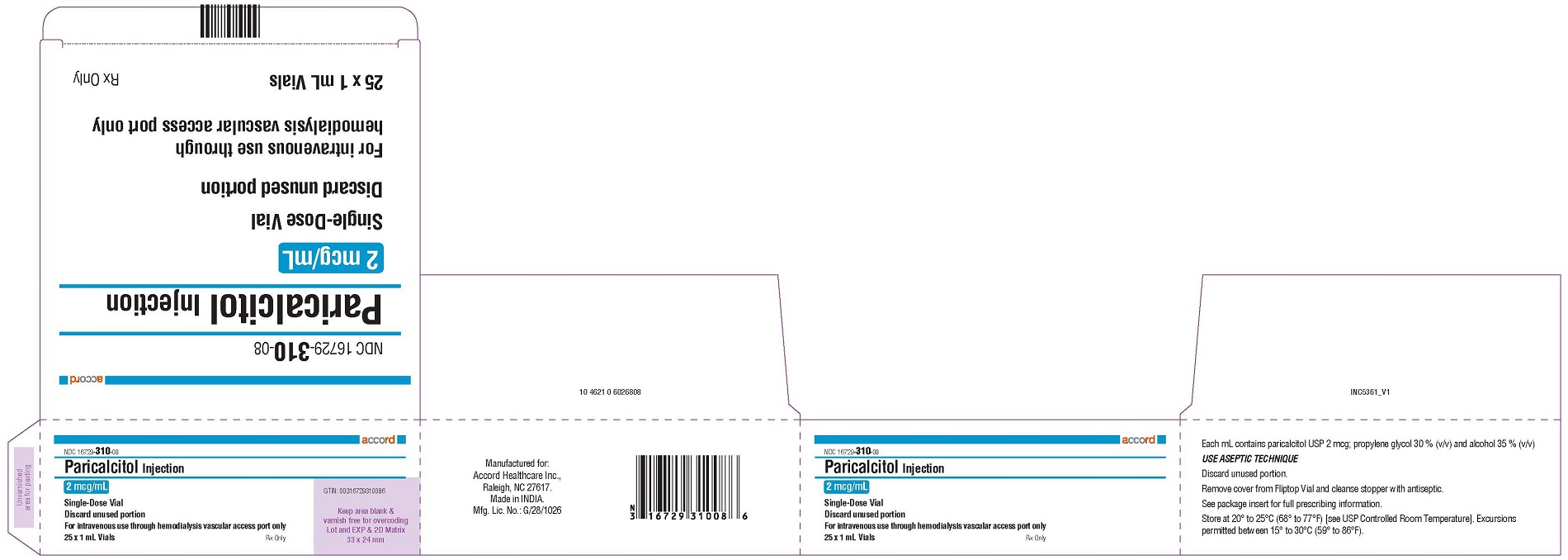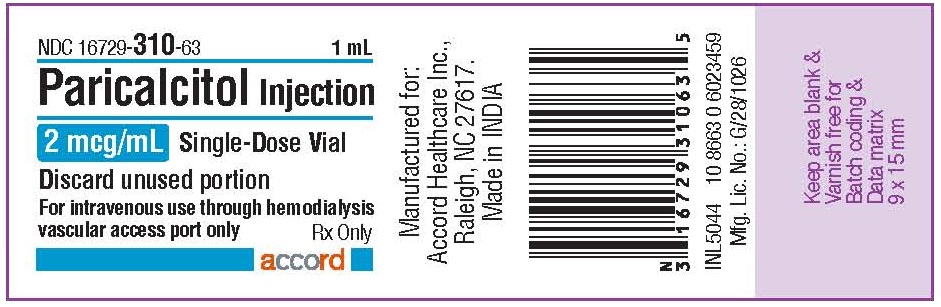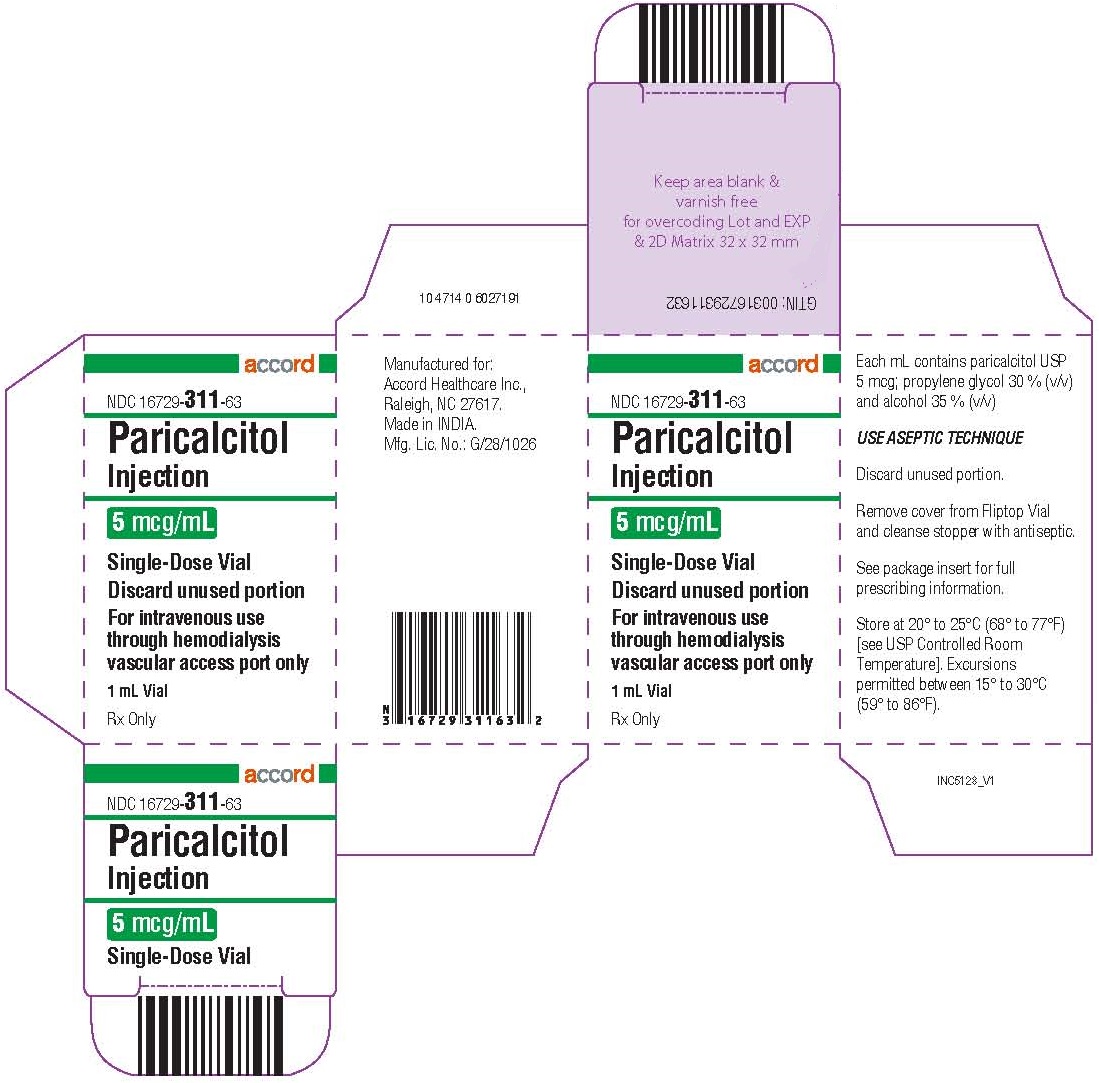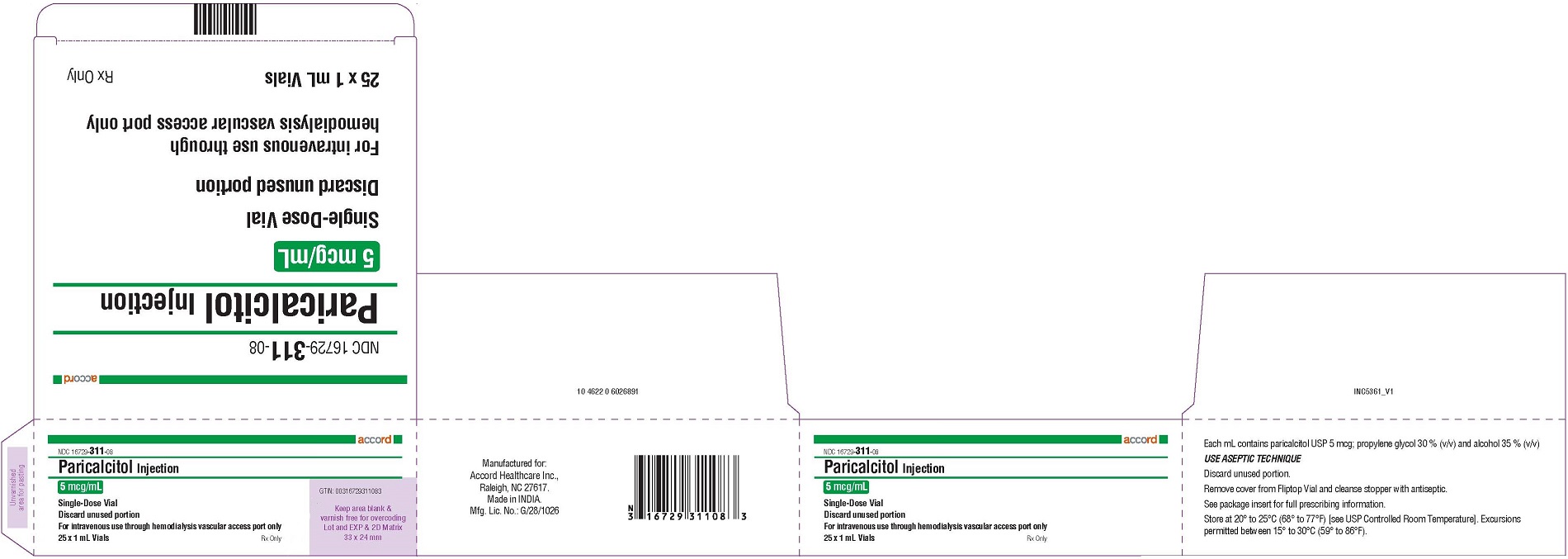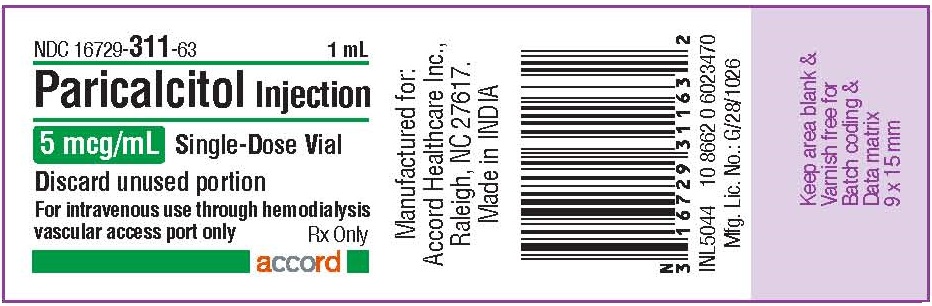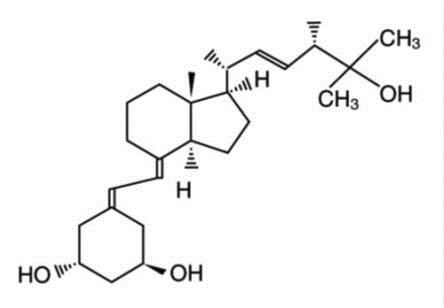 DRUG LABEL: Paricalcitol
NDC: 16729-310 | Form: INJECTION, SOLUTION
Manufacturer: Accord Healthcare, Inc.
Category: prescription | Type: HUMAN PRESCRIPTION DRUG LABEL
Date: 20240730

ACTIVE INGREDIENTS: PARICALCITOL 2 ug/1 mL
INACTIVE INGREDIENTS: PROPYLENE GLYCOL; ALCOHOL; WATER

HIGHLIGHTS OF PRESCRIBING INFORMATION

These highlights do not include all the information needed to use PARICALCITOL INJECTION safely and effectively. See full prescribing information for PARICALCITOL INJECTION.
PARICALCITOL injection, for intravenous use
Initial U.S. Approval: 1998

1 INDICATIONS AND USAGE

Paricalcitol Injection is a vitamin D analog indicated for the prevention and treatment of secondary hyperparathyroidism in patients 5 years of age and older with chronic kidney disease on dialysis.

2 DOSAGE AND ADMINISTRATION

- Ensure serum calcium is not above the upper limit of normal before initiating. (2.1)
- Administer Paricalcitol Injection intravenously through a hemodialysis vascular access at any time during dialysis. (2.1)
- Do not inject Paricalcitol Injection directly into a vein (2.1).

Adult Dose:

- Initiate at 0.04 mcg/kg to 0.1 mcg/kg (2.8 mcg to 7 mcg) no more frequently than every other day. (2.2)
- Target maintenance dose to intact parathyroid hormone (PTH) levels within the desired therapeutic range and serum calcium within normal limits. (2.2)
- Monitor serum calcium frequently (e.g., twice weekly) and intact PTH levels every 2 to 4 weeks after dose initiation or adjustment. (2.2)
- See Table 1 in the full prescribing information for titration recommendations based upon intact PTH levels. (2.2)
- Suspend or decrease the dose for persistent abnormally low intact PTH or serum calcium consistently above the normal range. (2.2)

Pediatric Dose:

- Initiate Paricalcitol Injection as an intravenous bolus dose of:
  - 0.04 mcg/kg if baseline intact PTH is less than 500 pg/mL, or
  - 0.08 mcg/kg if baseline intact PTH is 500 pg/mL or greater. (2.3)
- Target maintenance dose to intact PTH levels within the desired therapeutic range and serum calcium within normal limits. (2.3)
- Monitor serum calcium frequently (e.g., twice weekly) and intact PTH levels every 2 to 4 weeks after dose initiation or adjustment. (2.3)
- See Table 2 in the full prescribing information for titration recommendations based upon intact PTH levels. (2.3)
- Suspend or decrease the dose for persistent abnormally low intact PTH or serum calcium consistently above the normal range. (2.3)

3 DOSAGE FORMS AND STRENGTHS

Paricalcitol Injection is available as :

- Injection: 2 mcg/mL single-dose vial
- Injection: 5 mcg/mL single-dose vial
- Injection: 10 mcg/2 mL (5 mcg/mL) multiple-dose vial

4 CONTRAINDICATIONS

- Hypercalcemia (4)
- Vitamin D toxicity (4)
- Known hypersensitivity to paricalcitol or any other inactive ingredient. (4)

5 WARNINGS AND PRECAUTIONS

- Hypercalcemia:Can occur during treatment with Paricalcitol Injection and can lead to cardiac arrhythmias and seizures. Severe hypercalcemia may require emergency attention. The risk may be increased when Paricalcitol Injection is used concomitantly with high dose calcium preparations, thiazide diuretics, or vitamin D compounds. Inform patients about symptoms of hypercalcemia and monitor serum calcium prior to initiation and during treatment and adjust dose accordingly (2, 5.1).
- Digitalis Toxicity:Risk increases with hypercalcemia. In patients using digitalis compounds, monitor both serum calcium and patients for signs and symptoms of digitalis toxicity. Monitor more frequently when initiating or adjusting the dose of Paricalcitol Injection (5.2).
- Adynamic Bone Disease:May develop and increase risk of fractures if intact PTH levels are suppressed to abnormally low levels. Monitor intact PTH levels and adjust dose if needed (5.3).

6 ADVERSE REACTIONS

The most common adverse reactions (> 5% and more frequent than placebo) are nausea, vomiting and edema. (6.1)
To report SUSPECTED ADVERSE REACTIONS, contact Accord Healthcare Inc. at 1-866-941-7875 or FDA at 1-800-FDA-1088 or www.fda.gov/medwatch.

7 DRUG INTERACTIONS

Strong CYP3A Inhibitors:Co-administration with strong CYP3A inhibitors (e.g., ketoconazole) increases Paricalcitol Injection exposure. Dose adjustment may be necessary. Closely monitor intact PTH and serum calcium. (2.4, 7)

FULL PRESCRIBING INFORMATION

1 INDICATIONS AND USAGE

Paricalcitol Injection is indicated for the prevention and treatment of secondary hyperparathyroidism in patients 5 years of age and older with chronic kidney disease (CKD) on dialysis.

2 DOSAGE AND ADMINISTRATION

2.1 Important Administration Information

- Ensure serum calcium is not above the upper limit of normal before initiating treatment [see Warnings and Precautions (5.1)] .
- Administer Paricalcitol Injection intravenously through a hemodialysis vascular access port at any time during dialysis. Do not inject Paricalcitol Injection directly into a vein.
- Inspect Paricalcitol Injection visually prior to administration; the solution should appear clear and colorless. Do not use if the solution is not clear or particles are present.
- Discard unused portion of 2 mcg/mL and 5 mcg/mL single-dose vials.

2.2 Starting Dose and Dose Titration in Adults

- Initiate Paricalcitol Injection as an intravenous bolus dose of 0.04 mcg/kg to 0.1 mcg/kg (2.8 mcg to 7 mcg) no more frequently than every other day at any time during dialysis.
- Target the maintenance dose of Paricalcitol Injection to intact parathyroid hormone (PTH) levels within the desired therapeutic range and serum calcium within normal limits.
- Monitor serum calcium frequently (e.g., twice weekly) and intact PTH levels every 2 to 4 weeks after initiation of therapy or dose adjustment.
- Titrate the dose of Paricalcitol Injection based on intact PTH (see Table 1). Prior to raising the dose, ensure serum calcium is within normal limits. The maximum daily adult dose is 0.24 mcg/kg.
- Suspend or decrease the dose if intact PTH is persistently and abnormally low to reduce the risk of adynamic bone disease [see Warnings and Precautions (5.3)] or if serum calcium is consistently above the normal range to reduce the risk of hypercalcemia [see Warnings and Precautions (5.1)] . If dose suspension is necessary, restart at a reduced dose after laboratory values have normalized.

Table 1: Recommended Paricalcitol Injection Adult Dose Titration Based Upon intact PTH

Intact PTH Level At Follow-up Visit | Dosage Adjustment
Above target and intact PTH increased | Increase* by 2 mcg to 4 mcg every 2 to 4 weeks
Above target and intact PTH decreased by less than 30% | Increase* by 2 mcg to 4 mcg every 2 to 4 weeks
Above target and intact PTH decreased by 30% to 60% | No Change
Above target and intact PTH decreased by more than 60% | Decrease per clinical judgement
At target and intact PTH stable | No Change
* The maximum daily adult dose is 0.24 mcg/kg

2.3 Starting Dose and Dose Titration for Pediatric Patients 5 Years of Age and Above

- Initiate Paricalcitol Injection as an intravenous bolus dose of:
  - 0.04 mcg/kg if baseline intact PTH is less than 500 pg/mL, or
  - 0.08 mcg/kg if baseline intact PTH is 500 pg/mL or greater
- Administer Paricalcitol Injection three times per week, no more frequently than every other day, at any time during dialysis.
- Target the maintenance dose of Paricalcitol Injection to intact PTH levels within the desired therapeutic range and serum calcium within normal limits.
- Monitor serum calcium frequently (e.g., twice weekly) and intact PTH levels every 2 to 4 weeks after initiation of therapy or dose adjustment.
- Titrate the dose of Paricalcitol Injection based on intact PTH (see Table 2). Prior to raising the dose, ensure serum calcium is within normal limits.
- Suspend or decrease the dose if intact PTH is persistently and abnormally low to reduce the risk of adynamic bone disease [see Warnings and Precautions (5.3)] or if serum calcium is consistently above the normal range to reduce the risk of hypercalcemia [see Warnings and Precautions (5.1)] . If dose suspension is necessary, restart at a reduced dose after laboratory values have normalized.

Table 2: Recommended Paricalcitol Injection Pediatric Dose Titration Based Upon intact PTH – Patients 5 years of age and older

Intact PTH Level At Follow-up Visit | Dosage Adjustment
Above target and intact PTH decreased by less than 30% | Increase by 0.04 mcg/kg every 2 to 4 weeks
Intact PTH 150 pg/mL or greater and decreased by 30% to 60% | No Change
Intact PTH less than 150 pg/mL or decreased by more than 60% | Decrease by 0.04 mcg/kg weekly, or by 50% if decreased dose equals zero

2.4 Drug Interactions that May Require Dosage Adjustments of Paricalcitol Injection

- Increased monitoring of serum calcium and dose adjustment of Paricalcitol Injection may be necessary when given concomitantly with drugs that may increase the risk of hypercalcemia [see Drug Interactions (7)] .
- Increased monitoring of both serum calcium and intact PTH as well as dose adjustment of Paricalcitol Injection may be necessary when given concomitantly with strong CYP3A inhibitors [see Drug Interactions (7)] .

3 DOSAGE FORMS AND STRENGTHS

Injection: clear, colorless solution available as follows:

- 2 mcg/mL single-dose vial
- 5 mcg/mL single-dose vial
- 10 mcg/2 mL (5 mcg/mL) multiple-dose vial

4 CONTRAINDICATIONS

Paricalcitol Injection is contraindicated in patients with:

- Hypercalcemia [see Warnings and Precautions (5.1)]
- Vitamin D toxicity [see Warnings and Precautions (5.1)]
- Known hypersensitivity to paricalcitol or any of the inactive ingredients in Paricalcitol Injection. Hypersensitivity adverse reactions have been reported [e.g., angioedema (including laryngeal edema) and urticaria] [see Adverse Reactions (6.2)] .

5 WARNINGS AND PRECAUTIONS

5.1 Hypercalcemia

Hypercalcemia may occur during Paricalcitol Injection treatment. Acute hypercalcemia may increase the risk of cardiac arrhythmias and seizures and may potentiate the effect of digitalis on the heart [see Warnings and Precautions (5.2)] . Chronic hypercalcemia can lead to generalized vascular calcification and other soft-tissue calcification. Severe hypercalcemia may require emergency attention.

Hypercalcemia may be exacerbated by concomitant administration of high doses of calcium-containing preparations, thiazide diuretics, or other vitamin D compounds [see Drug Interactions (7)] . In addition, high intake of calcium and phosphate concomitantly with vitamin D compounds may lead to hypercalciuria and hyperphosphatemia. Patients with a history of hypercalcemia prior to initiating therapy may be at increased risk for development of hypercalcemia with Paricalcitol Injection. In these circumstances, frequent serum calcium monitoring and Paricalcitol Injection dose adjustments may be required.

When initiating Paricalcitol Injection or adjusting Paricalcitol Injection dose, measure serum calcium frequently (e.g., twice weekly). Once a maintenance dose has been established, measure serum calcium at least monthly. If hypercalcemia occurs, reduce the dose or discontinue Paricalcitol Injection until serum calcium is normal [see Dosage and Administration (2.2, 2.3)] .

Inform patients about the symptoms of elevated calcium (feeling tired, difficulty thinking clearly, loss of appetite, nausea, vomiting, constipation, increased thirst, increased urination and weight loss) and instruct them to report new or worsening symptoms when they occur.

5.2 Digitalis Toxicity

Paricalcitol Injection can cause hypercalcemia [see Warnings and Precautions (5.1)] which increases the risk of digitalis toxicity. In patients using Paricalcitol Injection concomitantly with digitalis compounds, monitor serum calcium and patients for signs and symptoms of digitalis toxicity. Increase the frequency of monitoring when initiating or adjusting the dose of Paricalcitol Injection [see Drug Interactions (7)] .

5.3 Adynamic Bone Disease

Adynamic bone disease with subsequent increased risk of fractures may develop if intact PTH levels are suppressed by Paricalcitol Injection to abnormally low levels. Monitor intact PTH levels to avoid over suppression and adjust Paricalcitol Injection dose, if needed [see Dosage and Administration (2.2, 2.3)] .

6 ADVERSE REACTIONS

The following serious adverse reactions are described below and elsewhere in the labeling:

- Hypercalcemia [see Warnings and Precautions (5.1)]
- Adynamic Bone Disease [see Warnings and Precautions (5.3)]

6.1 Clinical Trials Experience

Because clinical studies are conducted under widely varying conditions, adverse reaction rates observed in the clinical studies of a drug cannot be directly compared to rates in the clinical studies of another drug and may not reflect the rates observed in practice.

The safety of Paricalcitol Injection has been established from adequate and well-controlled studies of another paricalcitol injection product [see Clinical Studies (14)] . Below is a display of the adverse reactions of paricalcitol injection in these adequate and well-controlled studies.

Four placebo-controlled, double-blind, multicenter studies were conducted in 113 patients (51% male, 10% Caucasian, 81% African-American and 9% Hispanic, ranging in age from 18 to 90 years). Sixty-two patients were exposed to paricalcitol injection and the average dose at the end of treatment was 0.12 mcg/kg/dose with a mean number of 55 days of dosing across the studies. Discontinuation of therapy due to any adverse reaction occurred in 6.5% of patients treated with paricalcitol injection and 2.0% of patients treated with placebo. Adverse reactions occurring with greater frequency in the paricalcitol injection group and at a frequency of 2% or greater are presented in Table 3.

Table 3: Adverse Reactions Occurring at a Rate of 2% or Greater in Patients with CKD on Dialysis in Four Placebo-Controlled Studies

Adverse Reaction | Placebo (n = 51) % | Paricalcitol Injection (n = 62) %
Nausea | 8 | 13
Vomiting | 6 | 8
Edema | 0 | 7
Gastrointestinal Hemorrhage | 2 | 5
Chills | 2 | 5
Pyrexia | 2 | 5
Pneumonia | 0 | 5
Sepsis | 2 | 5
Influenza | 4 | 5
Arthralgia | 4 | 5
Palpitations | 0 | 3
Dry Mouth | 2 | 3
Malaise | 0 | 3

Other Adverse Reactions

The following adverse reactions occurred in less than 2% of the paricalcitol injection treated patients in the above mentioned studies and in additional double-blind, active-controlled and open-label studies:

Blood and Lymphatic System Disorders:Anemia, lymphadenopathy

Cardiac Disorders:Arrhythmia, atrial flutter, irregular heart rate, cardiac arrest, chest discomfort, chest pain, edema peripheral

Ear and Labyrinth Disorders:Ear discomfort

Endocrine Disorders:Hypoparathyroidism

Eye Disorders:Conjunctivitis, glaucoma, ocular hyperemia

Gastrointestinal Disorders:Abdominal discomfort, constipation, diarrhea, dysphagia, gastritis, intestinal ischemia, rectal hemorrhage

General Disorders:Asthenia, condition aggravated, fatigue, feeling abnormal, pain, swelling

Infections:Nasopharyngitis, upper respiratory tract infection, vaginal infection

Injection site reactions:Injection site extravasation, injection site pain

Laboratory abnormalities:Hypercalcemia, hyperkalemia, hyperphosphatemia, hypocalcemia, increased aspartate aminotransferase, prolonged bleeding time

Metabolism and Nutrition Disorders:Decreased appetite, thirst, decreased weight

Musculoskeletal and Connective Tissue Disorders:Joint stiffness, muscle twitching, myalgia

Neoplasms Benign, Malignant and Unspecified:Breast cancer

Nervous System Disorders:Cerebrovascular accident, dizziness, dysgeusia, headache, hypoesthesia, myoclonus, paresthesia, syncope, unresponsive to stimuli, gait disturbance

Psychiatric Disorders:Agitation, confusional state, delirium, insomnia, nervousness, restlessness

Reproductive System and Breast Disorders:Breast pain, erectile dysfunction

Respiratory, Thoracic and Mediastinal Disorders:Cough, dyspnea, orthopnea, pulmonary edema, wheezing

Skin and Subcutaneous Tissue Disorders:Alopecia, blister, hirsutism, night sweats, rash pruritic, pruritus, skin burning sensation

Vascular Disorders:Hypertension, hypotension

6.2 Postmarketing Experience

The following adverse reactions have been identified during post-approval use of Paricalcitol Injection. Because these reactions are reported voluntarily from a population of uncertain size, it is not always possible to reliably estimate their frequency or establish a causal relationship to drug exposure.

Allergic reactions, such as rash, urticaria, and angioedema (including laryngeal edema) have been reported.

7 DRUG INTERACTIONS

Table 4 includes clinically significant drug interactions with Paricalcitol Injection.

Table 4: Clinically Significant Drug Interactions with Paricalcitol Injection

Drugs that May Increase the risk of Hypercalcemia
Clinical Impact | Concomitant administration of high doses of calcium-containing preparations or other vitamin D compounds may increase the risk of hypercalcemia. Thiazide diuretics are known to induce hypercalcemia by reducing excretion of calcium in the urine.
Examples | Calcium-containing products, other vitamin D compounds or thiazide diuretics
Intervention | Monitor calcium more frequently and adjust Paricalcitol Injection dose as needed [see Warnings and Precautions (5.1)] .
Digitalis Compounds
Clinical Impact | Paricalcitol Injection can cause hypercalcemia which can potentiate the risk of digitalis toxicity.
Intervention | Monitor patients for signs and symptoms of digitalis toxicity and increase frequency of serum calcium monitoring when initiating or adjusting the dose of Paricalcitol Injection in patients receiving digitalis compounds [see Warnings and Precautions (5.2)] .
Strong CYP3A Inhibitors
Clinical Impact | Paricalcitol Injection is partially metabolized by CYP3A. Exposure of Paricalcitol Injection will increase upon coadministration with strong CYP3A inhibitors [see Clinical Pharmacology (12.3)] .
Examples | Clarithromycin, conivaptan, grapefruit juice, indinavir, itraconazole, ketoconazole, lopinavir/ritonavir, mibefradil, nefazodone, nelfinavir, posaconazole, ritonavir, saquinavir, and voriconazole
Intervention | If a patient initiates or discontinues therapy with a strong CYP3A4 inhibitor, dose adjustment of Paricalcitol Injection may be necessary. Monitor intact PTH and serum calcium concentrations closely.

8 USE IN SPECIFIC POPULATIONS

8.1 Pregnancy

Risk Summary

Limited data with Paricalcitol Injection in pregnant women are insufficient to inform a drug-associated risk for major birth defects and miscarriage. There are risks to the mother and fetus associated with chronic kidney disease in pregnancy (see Clinical Considerations).

In animal reproduction studies, slightly increased embryofetal loss was observed in pregnant rats and rabbits administered paricalcitol intravenously during the period of organogenesis at doses 2 and 0.5 times, respectively, a human dose of 14 mcg (equivalent to 0.24 mcg/kg), based on body surface area (mg/m^2). Adverse reproductive outcomes were observed at doses that caused maternal toxicity (see Data).

The estimated background risk of major birth defects and miscarriage for the indicated population is unknown. In the U.S. general population, the estimated background risk of major birth defects and miscarriage in clinically recognized pregnancies is 2% to 4% and 15% to 20%, respectively.

Clinical Considerations

Disease-Associated Maternal and/or Embryo/Fetal Risk

Chronic kidney disease in pregnancy increases the risk for maternal hypertension and preeclampsia, miscarriage, preterm delivery, polyhydramnios, still birth, and low birth weight infants.

Data

Animal Data

Pregnant rats and rabbits were treated with paricalcitol by once-daily intravenous injection during the period of organogenesis (in rats, from gestation day (GD) 6 to 17; in rabbits, from GD 6 to 18). Rats were dosed at 0, 0.3, 1 or 3 mcg/kg/day and rabbits at 0, 0.03, 0.1 or 0.3 mcg/kg/day, representing up to 2 or 0.5 times, respectively, a human dose of 0.24 mcg/kg, based on body surface area (mg/m^2). Slightly decreased fetal viability was observed in both studies at the highest doses representing 2 and 0.5 times, respectively, a human dose of 0.24 mcg/kg, in the presence of maternal toxicity (decreased body weight and food consumption). Pregnant rats were administered paricalcitol by intravenous injection three times per week at doses of 0, 0.3, 3 or 20 mcg/kg/day throughout gestation, parturition and lactation (GD 6 to lactation day (LD) 20) representing exposures up to 13 times a human dose of 0.24 mcg/kg. A small increase in stillbirths and pup deaths from parturition to LD 4 were observed at the high dose when compared to the control group (9.2% versus 3.3% in controls) at 13 times a human dose of 0.24 mcg/kg, which occurred at a maternally toxic dose known to cause hypercalcemia in rats. Surviving pups were not adversely affected; body weight gains, developmental landmarks, reflex ontogeny, learning indices, and locomotor activity were all within normal parameters. F1 reproductive capacity was unaffected.

8.2 Lactation

Risk Summary

There is no information available on the presence of paricalcitol in human milk, the effects of the drug on the breastfed infant or the effects of the drug on milk production. Studies in rats have shown that paricalcitol and/or its metabolites are present in the milk of lactating rats. When a drug is present in animal milk, it is likely that the drug will be present in human milk (see Data). Infants exposed to Paricalcitol Injection through breast milk should be monitored for signs and symptoms of hypercalcemia (see Clinical Considerations). The developmental and health benefits of breastfeeding should be considered along with the mother’s clinical need for Paricalcitol Injection and any potential adverse effects on the breast-fed child from Paricalcitol Injection or from the underlying maternal condition.

Clinical Considerations

Infants exposed to Paricalcitol Injection through breast milk should be monitored for signs and symptoms of hypercalcemia, including seizures, vomiting, constipation and weight loss. Monitoring of serum calcium in the infant should be considered.

Data

Following a single oral administration of 20 mcg/kg of radioactive [^3H] paricalcitol to lactating rats, the concentrations of total radioactivity was determined. Lower levels of total radioactivity were present in the milk compared to that in the plasma of the dams indicating that low levels of [^3H] paricalcitol and/or its metabolites are secreted into milk. Exposure of the pups to [^3H] paricalcitol through milk was confirmed by the presence of radioactive material in the pups’ stomachs.

8.4 Pediatric Use

The safety and efficacy of Paricalcitol Injection for the prevention and treatment of secondary hyperparathyroidism associated with CKD have been established in pediatric patients 5 years of age and older with CKD on dialysis. Use of Paricalcitol Injection for this indication is supported by evidence from an adequate and well-controlled study of another paricalcitol injection product in 29 patients, 5 to 19 years of age, with CKD on hemodialysis [see Clinical Studies (14)] .

The safety and efficacy of Paricalcitol Injection have not been established in pediatric patients less than 5 years old.

8.5 Geriatric Use

Clinical studies of paricalcitol injection did not include sufficient numbers of subjects aged 65 and over to determine whether they respond differently from younger subjects. Other reported clinical experience has not identified differences in responses between the elderly and younger patients. In general, dose selection for an elderly patient should be cautious, usually starting at the low end of the dosing range, reflecting the greater frequency of decreased hepatic or cardiac function, and of concomitant disease or other drug therapy.

8.6 Hepatic Impairment

The pharmacokinetics of paricalcitol were studied in patients with mild and moderate hepatic impairment and were similar to that of patients with normal hepatic function. No dose adjustment is required in patients with mild or moderate hepatic function.

Paricalcitol Injection has not been studied in patients with severe hepatic impairment.

10 OVERDOSAGE

Overdosage of Paricalcitol Injection may lead to hypercalcemia, hypercalciuria, and hyperphosphatemia [see Warnings and Precautions (5.1)] .

The treatment of acute overdosage should consist of supportive measures and discontinuation of drug administration. Serum calcium levels should be measured until normal.

Paricalcitol is not significantly removed by dialysis.

11 DESCRIPTION

Paricalcitol, USP, is a synthetically manufactured active vitamin D analog. It is a white powder chemically designated as 19-nor-1α,3β,25-trihydroxy-9,10-secoergosta-5(Z),7(E),22(E)-triene and has the following structural formula:

Molecular formula is C27H44O3.

Molecular weight is 416.64.

Paricalcitol Injection is a sterile, clear, colorless, aqueous solution for intravenous use. Each mL contains paricalcitol, 2 mcg or 5 mcg and the following inactive ingredients: alcohol, 35% (v/v) and propylene glycol, 30% (v/v).

12 CLINICAL PHARMACOLOGY

12.1 Mechanism of Action

Paricalcitol is a synthetic, biologically active vitamin D2analog. Preclinical and in vitrostudies have demonstrated that paricalcitol's biological actions are mediated through binding of the vitamin D receptor (VDR), which results in the selective activation of vitamin D responsive pathways. Vitamin D and paricalcitol have been shown to reduce PTH levels by inhibiting PTH synthesis and secretion.

12.3 Pharmacokinetics

Within two hours after administering paricalcitol injection intravenous doses ranging from 0.04 to 0.24 mcg/kg, concentrations of paricalcitol decreased rapidly; thereafter, concentrations of paricalcitol declined log-linearly. No accumulation of paricalcitol was observed with three times a week dosing.

Distribution

Paricalcitol is extensively bound to plasma proteins (≥99.8%). In healthy subjects, the steady-state volume of distribution is approximately 23.8 L. The mean volume of distribution following a 0.24 mcg/kg dose of paricalcitol in CKD Stage 5 subjects requiring hemodialysis (HD) and peritoneal dialysis (PD) is between 31 and 35 L.

Elimination

Metabolism

After intravenous administration of a 0.48 mcg/kg dose of^3H-paricalcitol, parent drug was extensively metabolized, with only about 2% of the dose eliminated unchanged in the feces and no parent drug found in the urine. Several metabolites were detected in both the urine and feces. Most of the systemic exposure was from the parent drug. Two minor metabolites, relative to paricalcitol, were detected in human plasma. One metabolite was identified as 24(R)-hydroxy paricalcitol, while the other metabolite was unidentified. The 24(R)-hydroxy paricalcitol is less active than paricalcitol in an in vivorat model of PTH suppression.

In vitrodata suggest that paricalcitol is metabolized by multiple hepatic and non-hepatic enzymes, including mitochondrial CYP24, as well as CYP3A4 and UGT1A4. The identified metabolites include the product of 24(R)-hydroxylation (present at low levels in plasma), as well as 24,26- and 24,28-dihydroxylation and direct glucuronidation.

Excretion

Paricalcitol is excreted primarily by hepatobiliary excretion. Approximately 63% of the radioactivity was eliminated in the feces and 19% was recovered in the urine in healthy subjects. In healthy subjects, the mean elimination half-life of paricalcitol is about five to seven hours over the studied dose range of 0.04 to 0.16 mcg/kg. The pharmacokinetics of paricalcitol has been studied in CKD patients requiring hemodialysis (HD) and peritoneal dialysis (PD). The mean elimination half-life of paricalcitol after administration of 0.24 mcg/kg paricalcitol IV bolus dose in CKD HD and PD patients is 13.9 and 15.4 hours, respectively (Table 5).

Table 5: Mean ± SD Paricalcitol Pharmacokinetic Parameters in CKD Patients on Dialysis Following Single 0.24 mcg/kg Intravenous Bolus Dose

 | CKD –HD (n=14) | CKD –PD (n=8)
Cmax(ng/mL) | 1.680 ± 0.511 | 1.832 ± 0.315
AUC0-∞(ng·h/mL) | 14.51 ± 4.12 | 16.01 ± 5.98
β (1/h) | 0.050 ± 0.023 | 0.045 ± 0.026
t1/2(h)* | 13.9 ± 7.3 | 15.4 ± 10.5
CL (L/h) | 1.49 ± 0.60 | 1.54 ± 0.95
Vdβ (L) | 30.8 ± 7.5 | 34.9 ± 9.5
* harmonic mean ± pseudo standard deviation, HD: hemodialysis, PD: peritoneal dialysis. The degree of accumulation was consistent with the half-life and dosing frequency.

Specific Populations

The pharmacokinetics of paricalcitol has not been investigated in geriatric and pediatric patients.

Male and Female Patients

The pharmacokinetics of paricalcitol were gender independent.

Patients with Hepatic Impairment

The disposition of paricalcitol (0.24 mcg/kg) was compared in patients with mild (n=5) and moderate (n=5) hepatic impairment (as indicated by the Child-Pugh method) and subjects with normal hepatic function (n=10). The pharmacokinetics of unbound paricalcitol were similar across the range of hepatic function evaluated in this study. The influence of severe hepatic impairment on the pharmacokinetics of paricalcitol has not been evaluated.

Patients with Renal Impairment

The pharmacokinetics of paricalcitol have been studied in CKD patients requiring hemodialysis (HD) and peritoneal dialysis (PD). Hemodialysis procedure has essentially no effect on paricalcitol elimination. However, compared to healthy subjects, CKD patients on dialysis showed a decreased CL and increased half-life.

Drug Interaction Studies

An in vitrostudy indicates that paricalcitol is not an inhibitor of CYP1A2, CYP2A6, CYP2B6, CYP2C8, CYP2C9, CYP2C19, CYP2D6, CYP2E1, or CYP3A at concentrations up to 50 nM (21 ng/mL) (approximately 20-fold greater than that obtained after highest tested dose). In fresh primary cultured hepatocytes, the induction observed at paricalcitol concentrations up to 50 nM was less than two-fold for CYP2B6, CYP2C9 or CYP3A, where the positive controls rendered a six- to nineteen-fold induction. Hence, paricalcitol is not expected to inhibit or induce the clearance of drugs metabolized by these enzymes.

Drug interactions with paricalcitol injection have not been studied. The following studies have been performed with oral paricalcitol capsules.

Omeprazole

The pharmacokinetic interaction between paricalcitol capsule (16 mcg) and omeprazole (40 mg; oral), a strong inhibitor of CYP2C19, was investigated in a single dose, crossover study in healthy subjects. The pharmacokinetics of paricalcitol were unaffected when omeprazole was administrated approximately 2 hours prior to the paricalcitol dose.

Strong CYP3A Inhibitors

Ketoconazole

The effect of multiple doses of ketoconazole, a strong inhibitor of CYP3A administered as 200 mg BID for 5 days, on the pharmacokinetics of paricalcitol capsule has been studied in healthy subjects. The Cmaxof paricalcitol was minimally affected, but AUC0-∞approximately doubled in the presence of ketoconazole. The mean half-life of paricalcitol was 17.0 hours in the presence of ketoconazole as compared to 9.8 hours, when paricalcitol was administered alone [see Drug Interactions (7)] .

13 NONCLINICAL TOXICOLOGY

13.1 Carcinogenesis, Mutagenesis and Impairment of Fertility

In a 104-week carcinogenicity study in CD-1 mice, an increased incidence of uterine leiomyoma and leiomyosarcoma was observed at subcutaneous doses of 1, 3, 10 mcg/kg administered 3 times per week (2 to 15 times the AUC at a human dose of 14 mcg, equivalent to 0.24 mcg/kg based on AUC). The incidence rate of uterine leiomyoma was significantly different than the control group at the highest dose of 10mcg/kg.

In a 104-week carcinogenicity study in rats, there was an increased incidence of benign adrenal pheochromocytoma at subcutaneous doses of 0.15, 0.5, 1.5 mcg/kg administered 3 times per week (at less than clinical exposure to 7 times the exposure following a human dose of 14 mcg, equivalent to 0.24 mcg/kg based on AUC). The increased incidence of pheochromocytomas in rats may be related to the alteration of calcium homeostasis by paricalcitol.

Paricalcitol did not exhibit genetic toxicity in vitrowith or without metabolic activation in the microbial mutagenesis assay (Ames Assay), mouse lymphoma mutagenesis assay (L5178Y), or a human lymphocyte cell chromosomal aberration assay. There was also no evidence of genetic toxicity in an in vivomouse micronucleus assay.

Paricalcitol had no effect on fertility (male or female) in rats at intravenous doses up to 20 mcg/kg/dose (13 times a human dose of 14 mcg, equivalent to 0.24 mcg/kg based on surface area, mg/m^2).

14 CLINICAL STUDIES

The safety and efficacy of Paricalcitol Injection have been established based on adult studies of another paricalcitol injection product in patients with CKD on hemodialysis. Below is a display of the results of these studies of paricalcitol injection.

Adult Studies in CKD on Dialysis

Three 12-week, placebo-controlled studies were conducted in 78 patients with CKD on hemodialysis. In these studies, patients ranged in age from 22 to 90 years, 51% were males, 13% were Caucasian, 79% were African-American, and 8% were Hispanic. The most common causes of renal failure were hypertension and diabetes. The dose of paricalcitol injection was started at 0.04 mcg/kg 3 times per week intravenously. The dose was increased by 0.04 mcg/kg every 2 weeks until intact PTH levels were decreased at least 30% from baseline or a fifth escalation brought the dose to 0.24 mcg/kg, or intact PTH fell to less than 100 pg/mL, or the Ca × P product was greater than 75 within any 2 week period, or serum calcium became greater than 11.5 mg/dL at any time.

Patients treated with paricalcitol injection achieved a mean intact PTH reduction of 30% within 6 weeks. The results from these studies are as follows:

Table 6: Mean Changes from Baseline to Final Evaluation in intact PTH, Alkaline Phosphatase, Phosphorus and Calcium × Phosphorus Product in Adult Patients with CKD on Dialysis in Three 12-Week Placebo-Controlled Studies

 | Group (No. of Pts.) | Baseline Mean (Range) | Mean (SE) Change From Baseline to Final Evaluation
intact PTH (pg/mL) | Paricalcitol Injection (n = 40) | 783 (291 - 2076) | -379 (43.7)
intact PTH (pg/mL) | placebo (n = 38) | 745 (320 - 1671) | -69.6 (44.8)
Alkaline Phosphatase (U/L) | Paricalcitol Injection (n = 31) | 150 (40 - 600) | -41.5 (10.6)
Alkaline Phosphatase (U/L) | placebo (n = 34) | 169 (56 - 911) | +2.6 (10.1)
Phosphorus (mg/dL) | Paricalcitol Injection (n = 40) | 5.8 (3.7 - 10.2) | +0.47 (0.3)
Phosphorus (mg/dL) | placebo (n = 38) | 6.0 (2.8 - 8.8) | -0.47 (0.3)
Calcium × Phosphorus Product | Paricalcitol Injection (n = 40) | 54 (32 - 106) | +7.9 (2.2)
Calcium × Phosphorus Product | placebo (n = 38) | 54 (26 - 77) | -3.9 (2.3)

Pediatric Study in CKD on Dialysis

Paricalcitol Injection was evaluated in a 12-week randomized, double-blind, placebo-controlled study of 29 pediatric patients, aged 5 to 19 years, with CKD on hemodialysis; nearly all had received some form of vitamin D prior to the study. Of the 29 patients, 76% were male, 52% were Caucasian and 45% were African-American. The initial dose of paricalcitol injection was 0.04 mcg/kg 3 times per week, based on baseline intact PTH level of less than 500 pg/mL, or 0.08 mcg/kg 3 times per week, based on baseline intact PTH level of 500 pg/mL or greater. The dose of paricalcitol injection was adjusted in 0.04 mcg/kg increments based on the levels of serum intact PTH, calcium and Ca × P. The mean baseline levels of intact PTH were 841 pg/mL for the 15 patients treated with paricalcitol injection and 740 pg/mL for the 14 placebo-treated patients. The mean dose of paricalcitol injection administered was 4.6 mcg (range: 0.8 mcg to 9.6 mcg). Sixty-seven percent of the patients treated with paricalcitol injection and 14% of the placebo-treated patients completed the trial. Seventy-one percent of the placebo-treated patients discontinued due to excessive elevations in intact PTH levels, as defined by 2 consecutive intact PTH levels greater than 700 pg/mL and greater than baseline after 4 weeks of treatment.

The primary efficacy analysis demonstrated that 60% of patients treated with paricalcitol injection and 21% of placebo-treated patients achieved two consecutive greater than or equal to 30% reductions from baseline in intact PTH.

16 HOW SUPPLIED/STORAGE AND HANDLING

Paricalcitol Injection is a clear, colorless solution available as follows:

Table 7. Paricalcitol Injection Presentations – Carton of 1 vial

Total Strength per Total Volume | Strength per mL | Total Vial Volume and Vial Type | NDC
2 mcg/mL | 2 mcg/mL | 1 mL single-dose vial | 16729-310-63
5 mcg/mL | 5 mcg/mL | 1 mL single-dose vial | 16729-311-63
10 mcg/2 mL | 5 mcg/mL | 2 mL multiple-dose vial | 16729-311-30

Table 8. Paricalcitol Injection Presentations – Carton of 25 vials

Total Strength per Total Volume | Strength per mL | Total Vial Volume and Vial Type | NDC
2 mcg/mL | 2 mcg/mL | 1 mL single-dose vial | 16729-310-08
5 mcg/mL | 5 mcg/mL | 1 mL single-dose vial | 16729-311-08
10 mcg/2 mL | 5 mcg/mL | 2 mL multiple-dose vial | 16729-311-93

Storage

Store at 20° to 25°C (68° to 77°F) [see USP Controlled Room Temperature]. Excursions permitted between 15° to 30°C (59° to 86°F).
Discard unused portion of the single-dose vial.
The opened (in use) multiple-dose vial should be stored at room temperature 20°C to 25°C (68° to 77°F) and protected from light. Discard seven days after opening.

17 PATIENT COUNSELING INFORMATION

Hypercalcemia

Advise patients to contact a health care provider if they develop symptoms of elevated calcium (e.g. feeling tired, difficulty thinking clearly, loss of appetite, nausea, vomiting, constipation, increased thirst, increased urination and weight loss) [see Warnings and Precautions (5.1)] .

Monitoring

Inform patients that they will need routine monitoring of laboratory parameters such as calcium and intact PTH while receiving Paricalcitol Injection. Inform patients that more frequent monitoring is necessary during the initiation of therapy, following dose changes or when potentially interacting medications are started or discontinued [see Dosage and Administration (2), Drug Interactions (7)] .

Drug Interactions

Advise patients to inform their physician of all medications, including prescription and nonprescription drugs, and supplements they are taking. Advise patients to also inform their physician that they are receiving Paricalcitol Injection if a new medication is prescribed [see Drug Interactions (7)] .

Manufactured For:
Accord Healthcare, Inc.,
8041 Arco Corporate Drive,
Suite 200,
Raleigh, NC 27617,
USA.

Manufactured By:
Intas Pharmaceuticals Limited,
Plot No. : 457, 458,
Village – Matoda,
Bavla Road, Ta.- Sanand,
Dist. Ahmedabad - 382 210,
India.

10 0246 2 6027315

Issued December, 2023

PRINCIPAL DISPLAY PANEL

Paricalcitol Injection 2mcg/ml-Label

Paricalcitol Injection 2mcg/ml- 1 vial Carton

Paricalcitol Injection 2mcg/ml- 25 vial Carton

Paricalcitol Injection 5mcg/ml-Label

Paricalcitol Injection 5mcg/ml- 1 vial Carton

Paricalcitol Injection 5mcg/ml- 25 vial Carton

Paricalcitol Injection 10mcg/2ml-Label

Paricalcitol Injection 10mcg/2ml- 1 vial Carton

Paricalcitol Injection 10mcg/2ml- 25 vial Carton